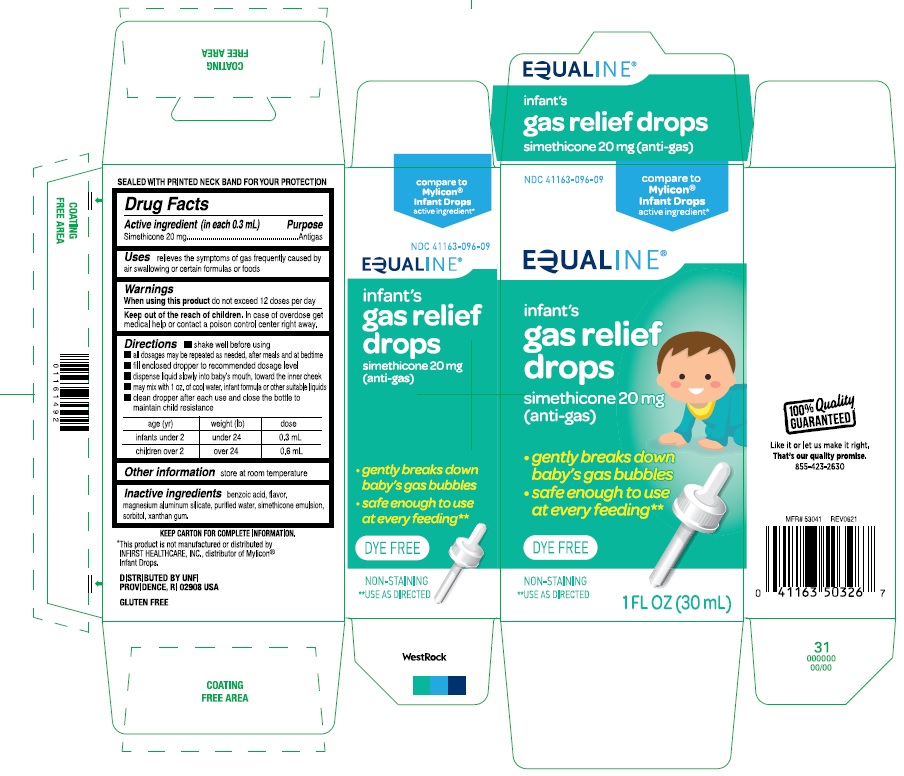 DRUG LABEL: Infants Gas relief
NDC: 41163-096 | Form: SOLUTION/ DROPS
Manufacturer: UNITED NATURAL FOODS, INC. DBA UNFI
Category: otc | Type: Human OTC Drug Label
Date: 20241220

ACTIVE INGREDIENTS: DIMETHICONE 20 mg/0.3 mL
INACTIVE INGREDIENTS: BENZOIC ACID; MAGNESIUM ALUMINUM SILICATE; WATER; SORBITOL; XANTHAN GUM

Equaline Infant's Gas Relief Drops

ACTIVE INGREDIENT (in each 0.3 mL)

Simethicone 20 mg

PURPOSE

Antigas

USE(S)

relieves the symptoms of gas frequently caused by air swallowing or certain formulas or foods

WARNINGS

.

WHEN USING THIS PRODUCT

do not exceed 12 doses per day

KEEP OUT OF THE REACH OF CHILDREN

In case of overdose get medical help or contact a poison control center right away

DIRECTIONS

- shake well before using
- all dosages may be repeated as needed, after meals and at bedtime
- fill enclosed dropper to recommended dosage level
- dispense liquid slowly into baby's mouth, toward the inner cheek
- may mix with 1 oz. of cool water, infant formula or other suitable liquids
- clean dropper after each use and close the bottle to maintain child resistance

age (yr) | weight (lb) | dose
infants under 2 | under 24 | 0.3 mL
children over 2 | over 24 | 0.6 mL

OTHER INFORMATION

store at room temperature

INACTIVE INGREDIENTS

benzoic acid, flavor, magnesium aluminum silicate, purified water, simethicone emulsion, sorbitol, xanthan gum

PRINCIPAL DISPLAY PANEL

Compare to Mylicon® infant drops active ingredient*

NDC 41163-096-09

EQUALINE

infants'

gas relief

drops

simethicone 20 mg

(anti-gas)

- gently breaks down baby's gas bubbles
- safe enough to use at every feeding**

DYE-FREE

NON-STAINING

**USE AS DIRECTED

1 FL OZ (30 mL)